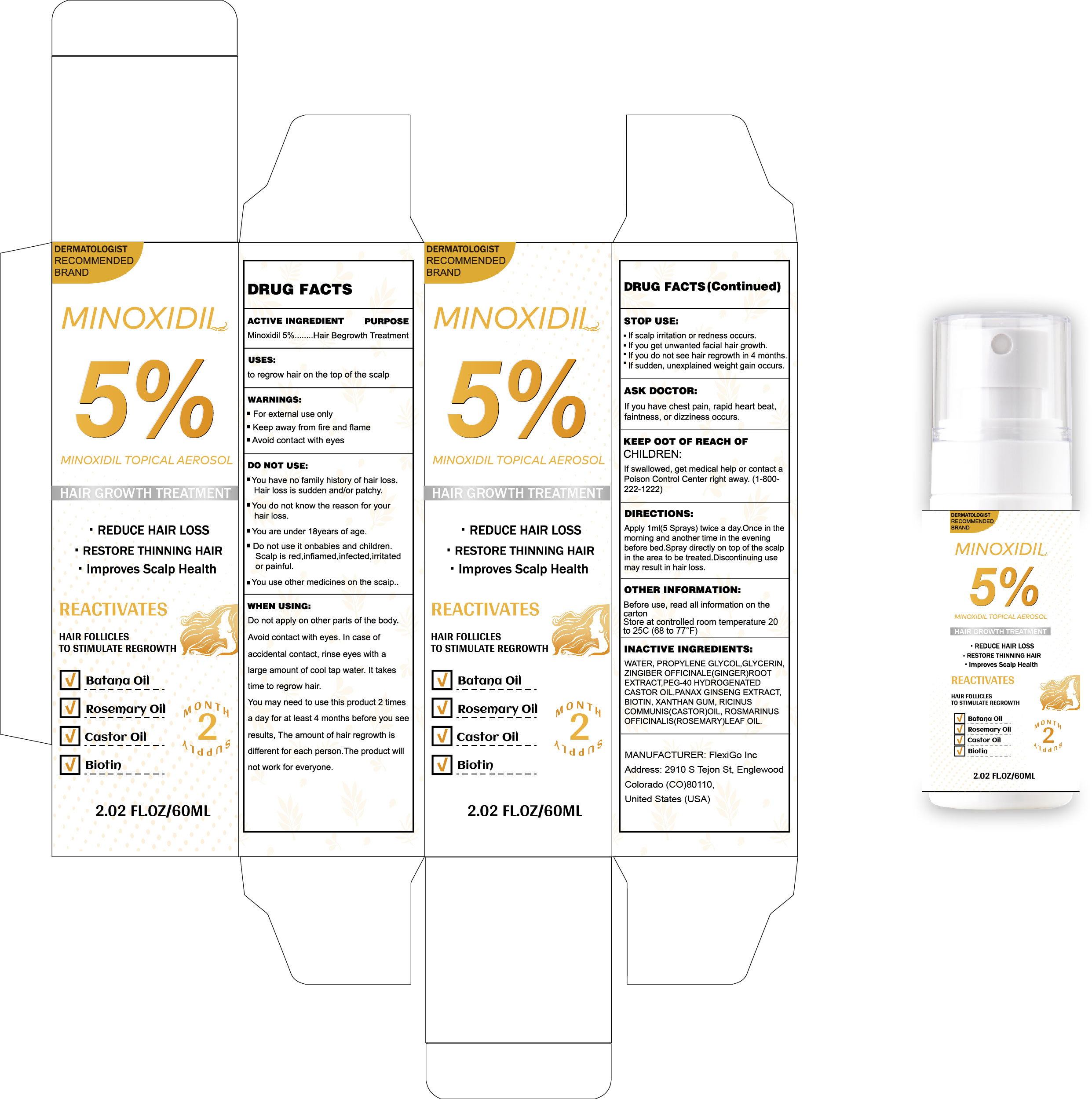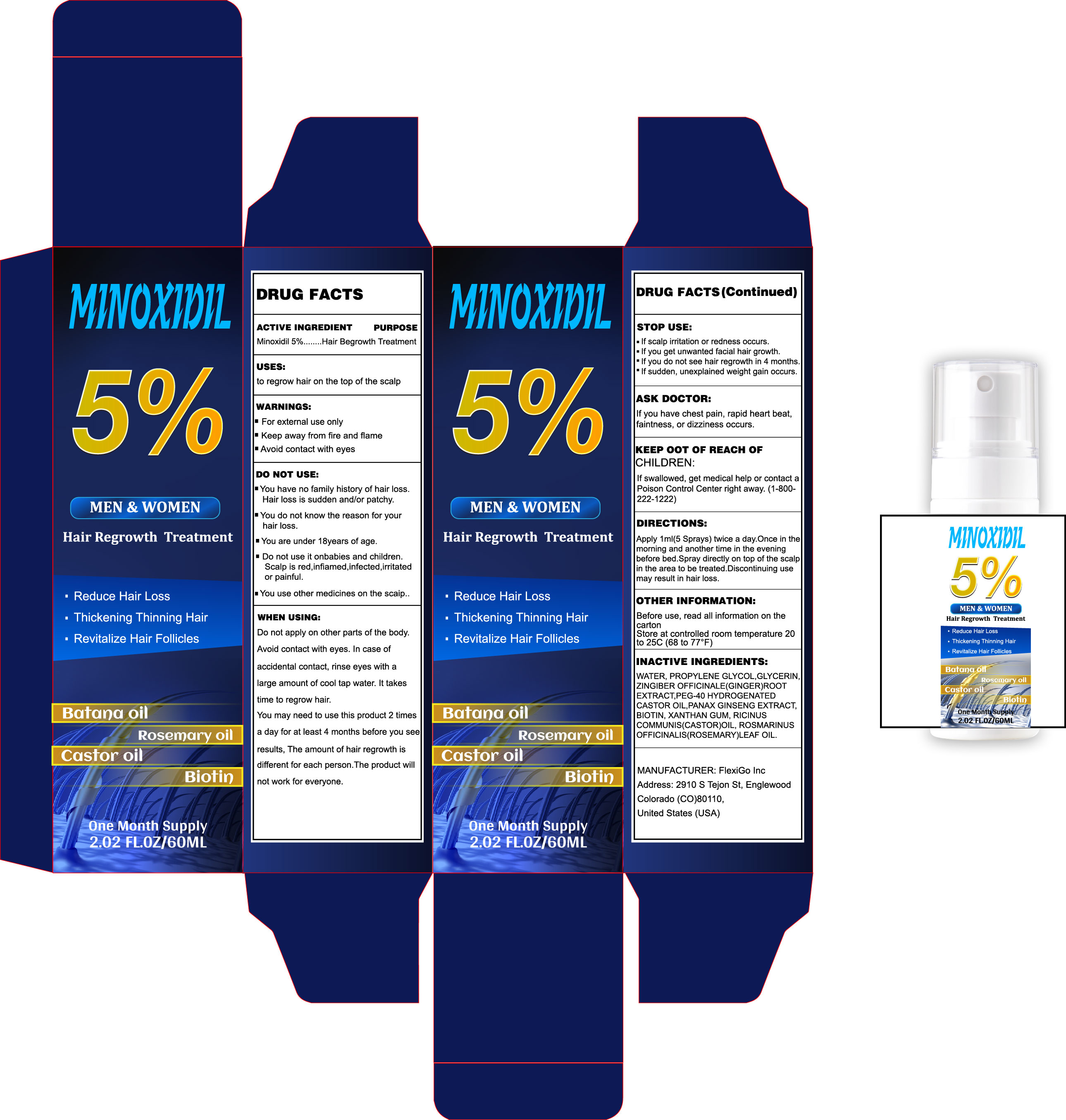 DRUG LABEL: MINOXIDIL
NDC: 85524-2501 | Form: LIQUID
Manufacturer: FlexiGo Inc
Category: otc | Type: HUMAN OTC DRUG LABEL
Date: 20250917

ACTIVE INGREDIENTS: MINOXIDIL 5 g/100 mL
INACTIVE INGREDIENTS: PROPYLENE GLYCOL; CASTOR OIL; PEG-40 HYDROGENATED CASTOR OIL; XANTHAN GUM; GLYCERIN; ROSEMARY OIL; PANAX NOTOGINSENG ROOT

DOSAGE AND ADMINISTRATION